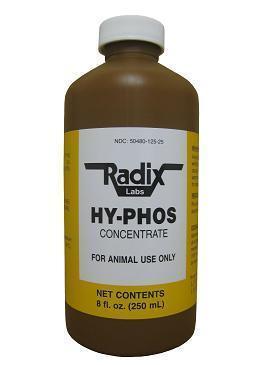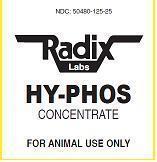 DRUG LABEL: HYPHOS CONCENTRATE
NDC: 50480-125 | Form: LIQUID
Manufacturer: Radix Laboratories, Inc.
Category: animal | Type: OTC ANIMAL DRUG LABEL
Date: 20140127

ACTIVE INGREDIENTS: HEXASODIUM HEXAMETAPHOSPHATE 28 g/250 mL

HYPHOS CONCENTRATE

• CONTENTS (per ml):

- 6,2 Phosphate Sodium .....113mg

Inactives:

- Purified Water q.s.
- Preservative: Methylparaben, Propylparaben

MEq VALUES

- Sodium ...............275 MEq
- Phosphate .........275 MEq

Indications:

- For use as a supplemental nutritive source of phosphorus in cattle.

Storage:

- Store at controlled room temperature between 59oF to 86oF (15oC -30oC).

Warnings:

- Avoid storage at cold temperatures which can cause product to become cloudy.
- To clarify place product in warm water bath (100oF-120oF) for about 30 minutes.

Dosage and administration:

- Administer orally as a drench or by use of a stomach tube.
- The usual recommended dose in adult cattle is 5 fl. oz (150mL) to 8 fl.oz (250mL) depending on size and condition.

- Keep away from children.